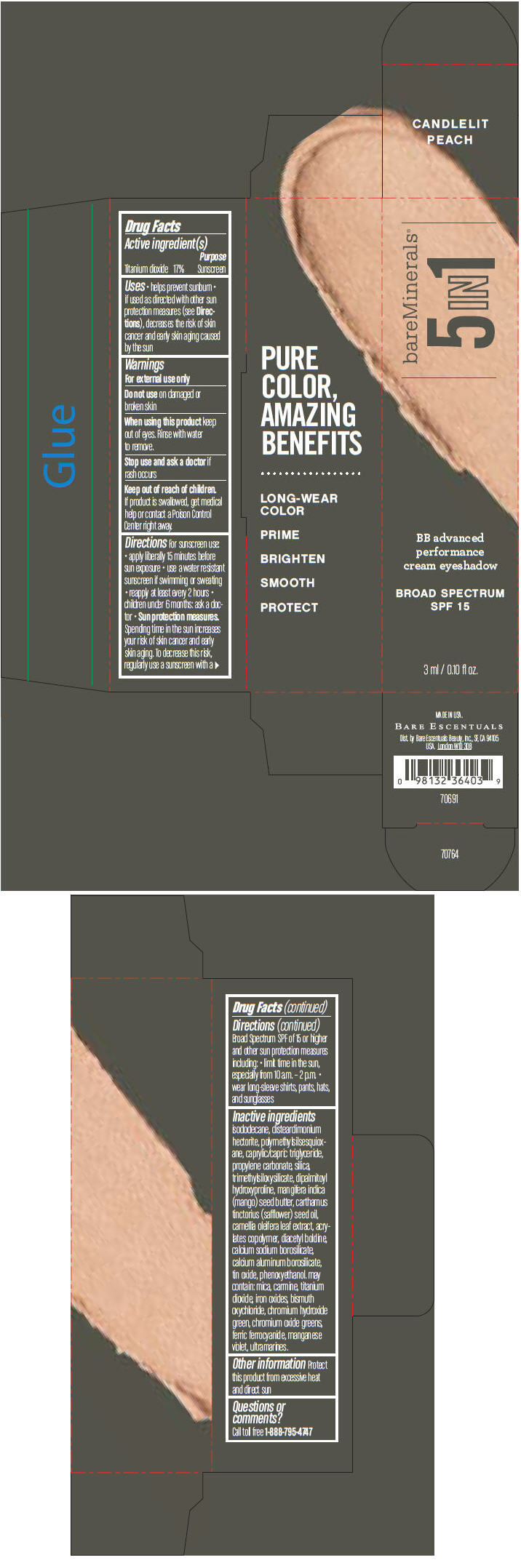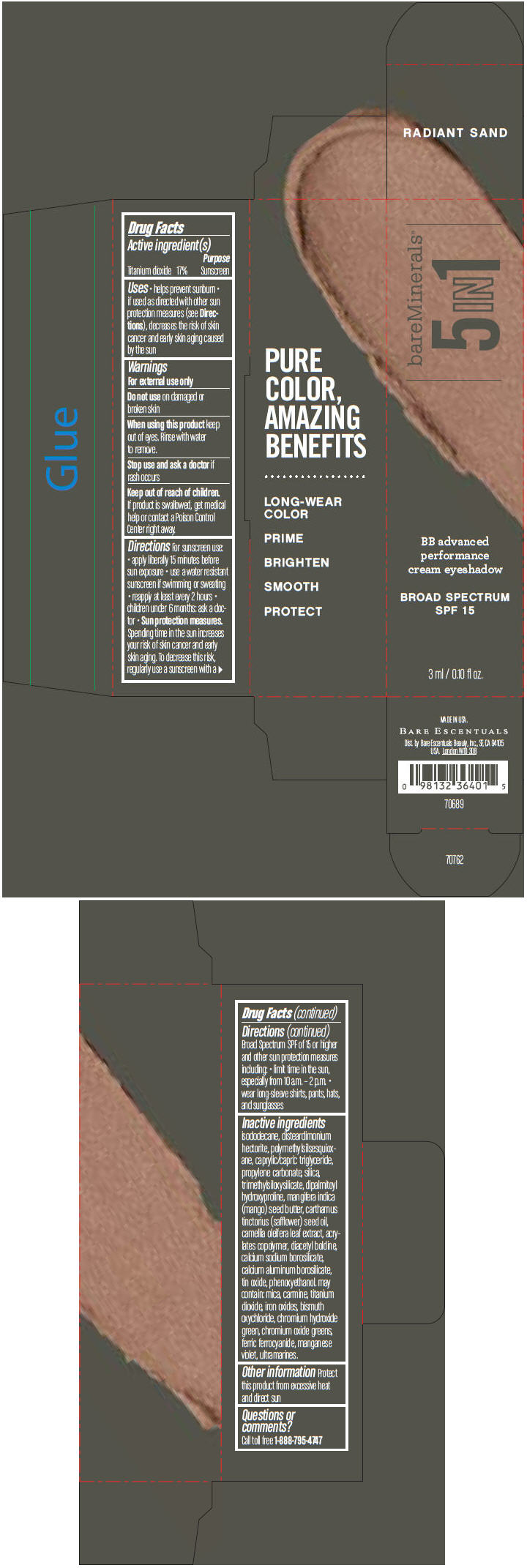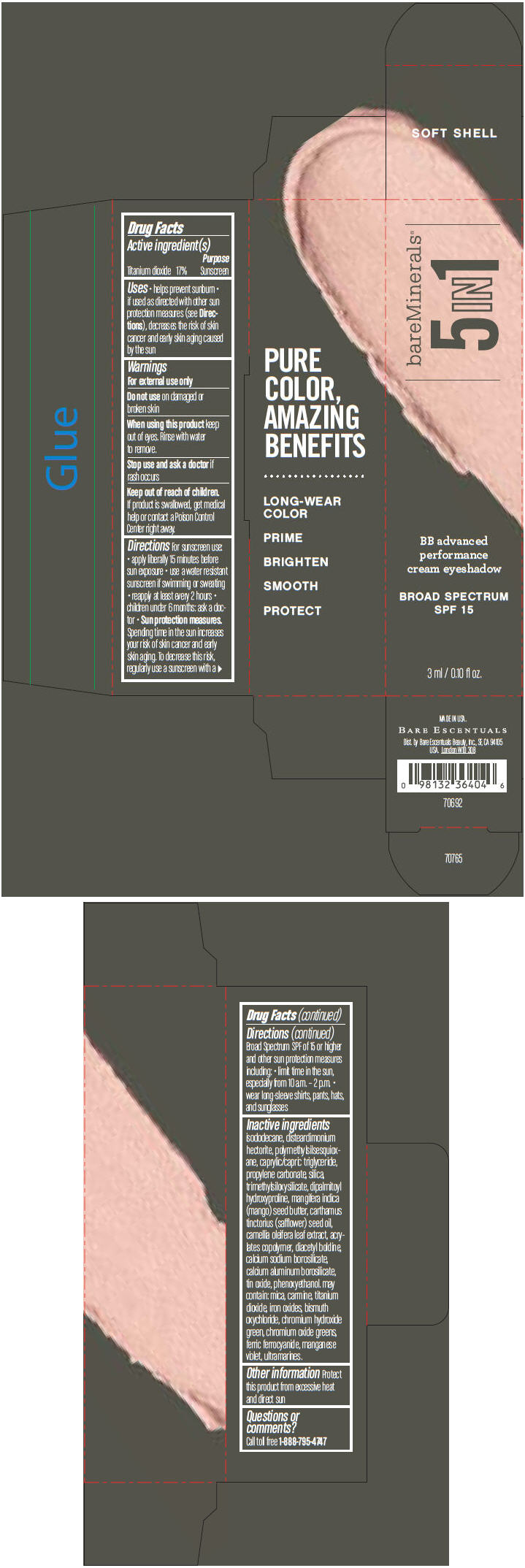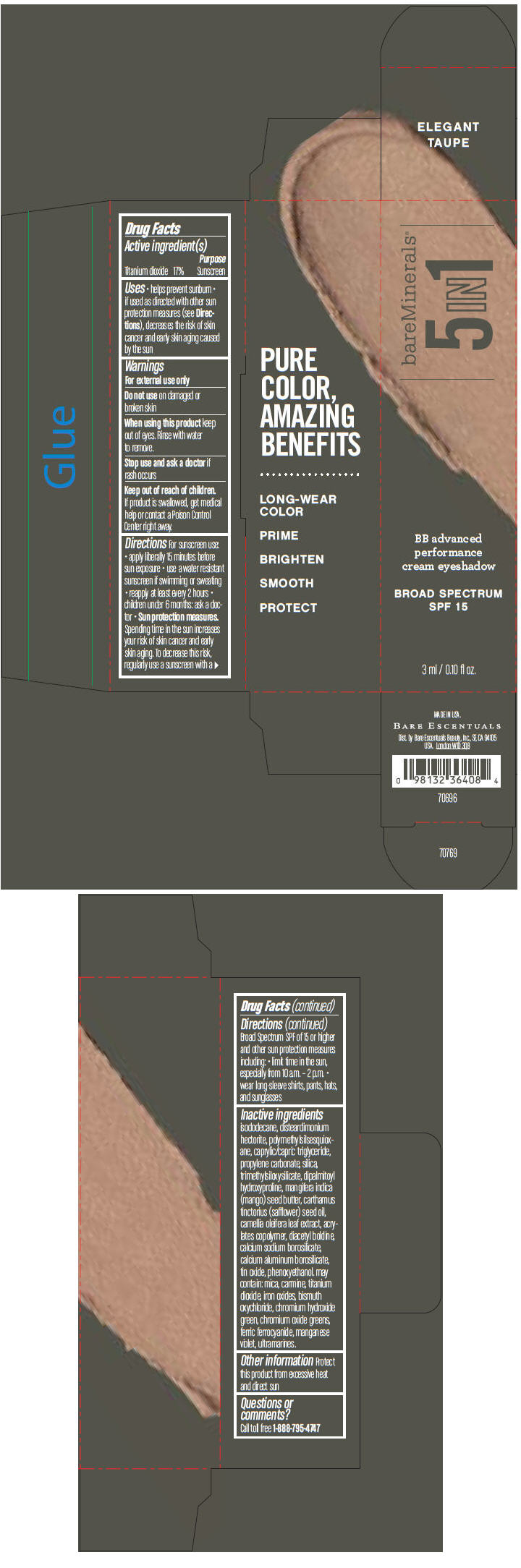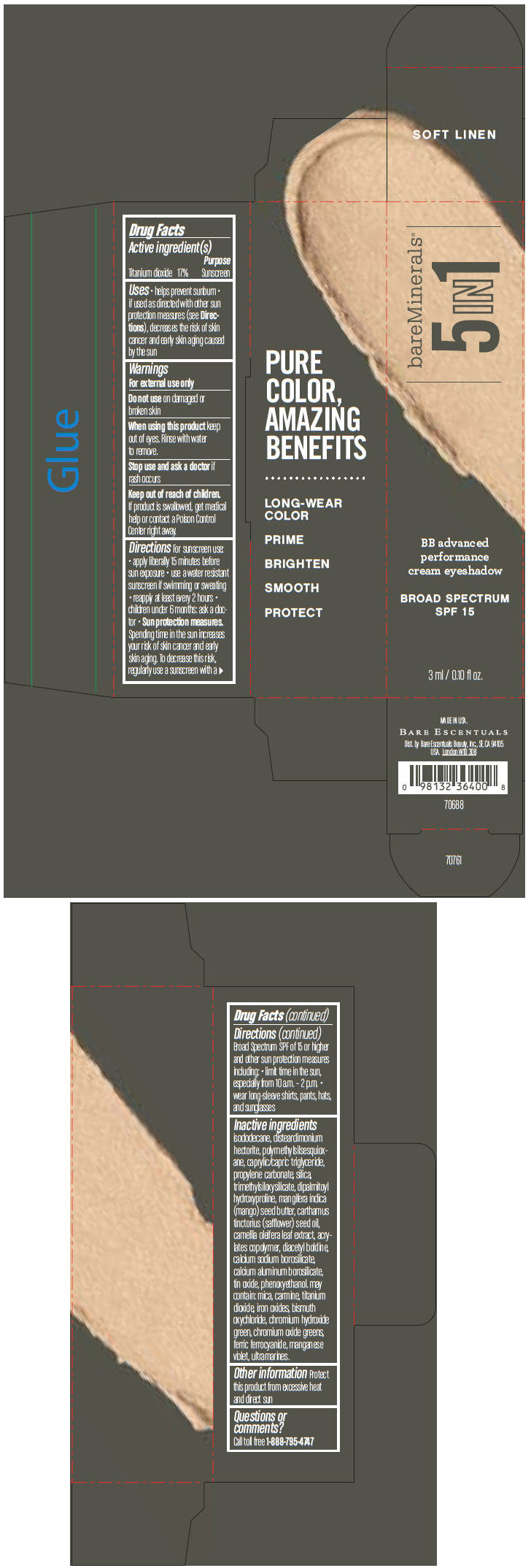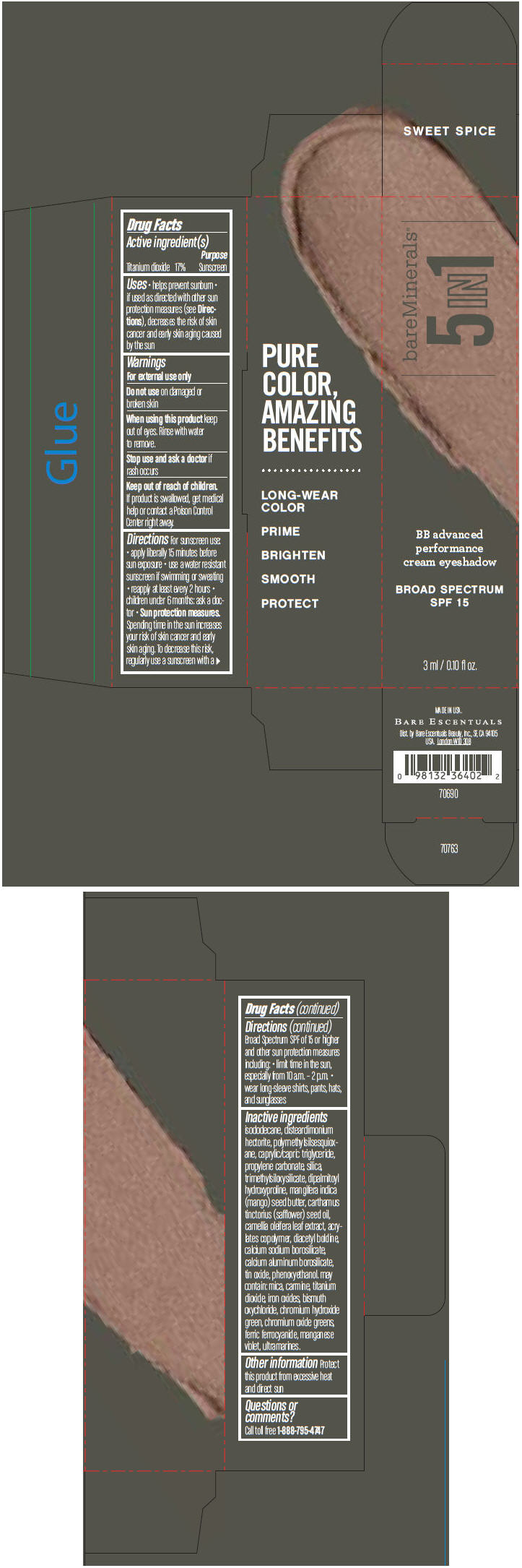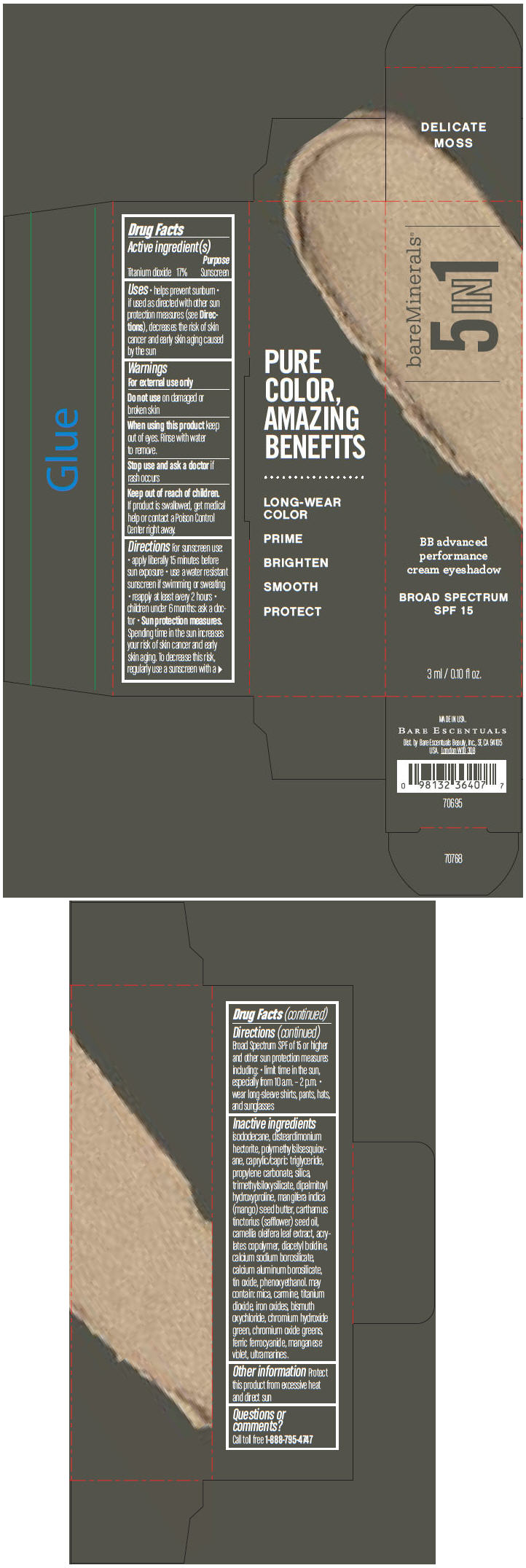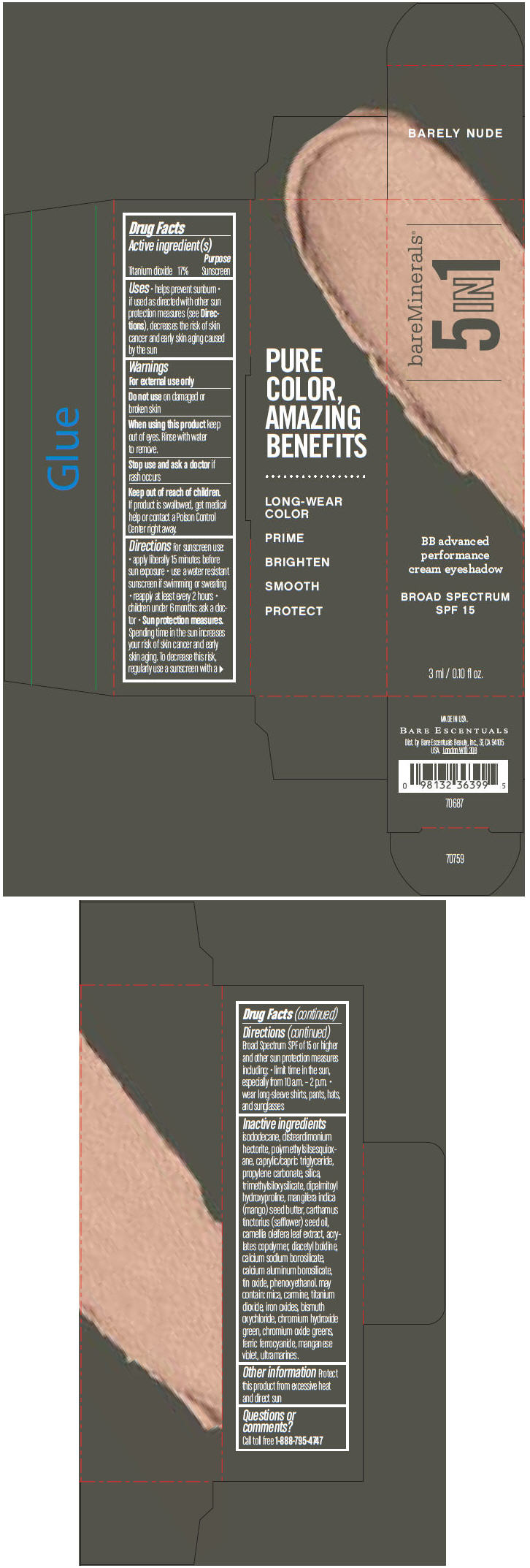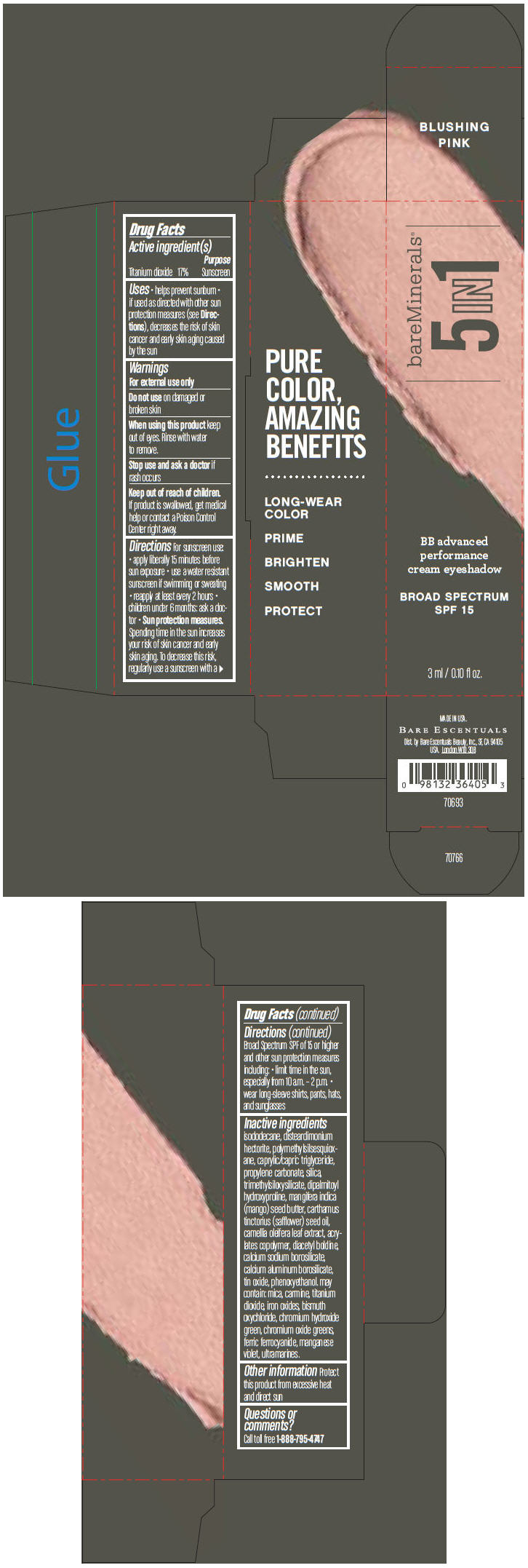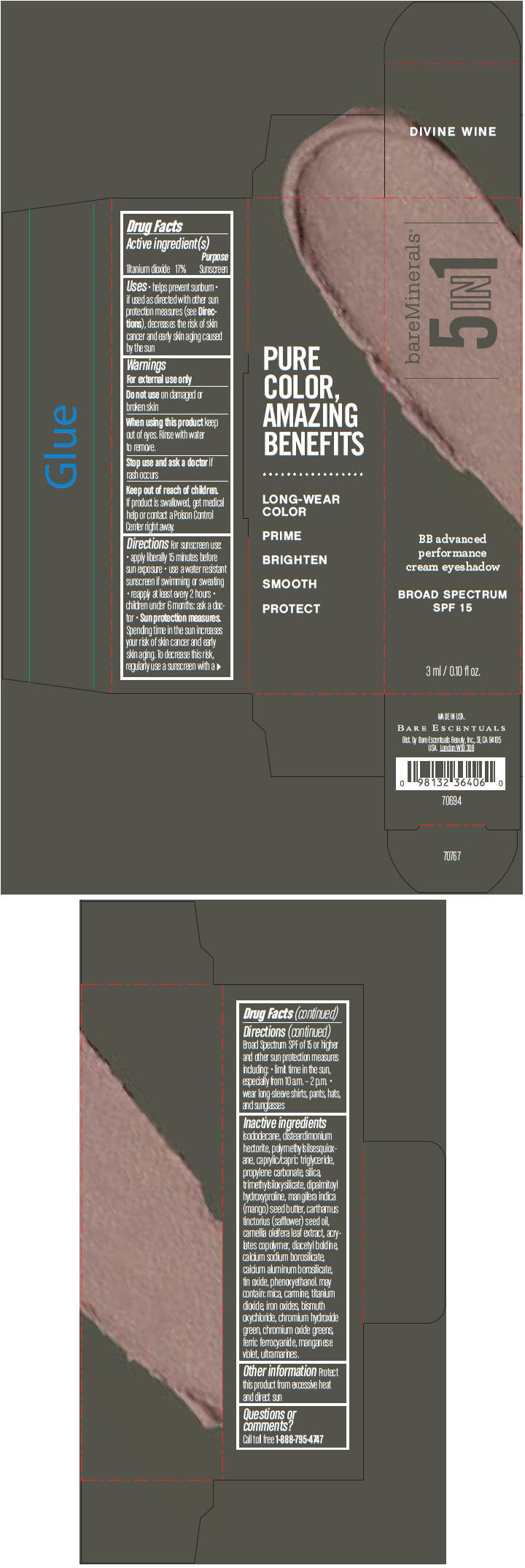 DRUG LABEL: bareMinerals 5-in-1 BB Advanced Performance Eyeshadow Broad Spectrum SPF 15 
NDC: 98132-700 | Form: CREAM
Manufacturer: Bare Escentuals Beauty, Inc.
Category: otc | Type: HUMAN OTC DRUG LABEL
Date: 20140128

ACTIVE INGREDIENTS: Titanium Dioxide 170 mg/1 mL
INACTIVE INGREDIENTS: ISODODECANE; DISTEARDIMONIUM HECTORITE; MEDIUM-CHAIN TRIGLYCERIDES; PROPYLENE CARBONATE; SILICON DIOXIDE; DIPALMITOYL HYDROXYPROLINE; MANGIFERA INDICA SEED BUTTER; SAFFLOWER OIL; CAMELLIA OLEIFERA LEAF; DIACETYL BOLDINE; CALCIUM ALUMINUM BOROSILICATE; STANNIC OXIDE; PHENOXYETHANOL; MICA; FERRIC OXIDE RED; BISMUTH OXYCHLORIDE; CHROMIUM HYDROXIDE GREEN; CHROMIC OXIDE; FERRIC FERROCYANIDE; MANGANESE VIOLET

bareMinerals® 5-in-1 BB Advanced Performance Cream Eyeshadow Broad Spectrum SPF 15

Drug Facts

Active ingredient(s)

Titanium dioxide 17%

Purpose

Sunscreen

Uses

- helps prevent sunburn
- if used as directed with other sun protection measures (see Directions), decreases the risk of skin cancer and early skin aging caused by the sun

Warnings

For external use only

Do not use on damaged or broken skin

When using this product keep out of eyes. Rinse with water to remove.

Stop use and ask a doctor if rash occurs

Keep out of reach of children. If product is swallowed, get medical help or contact a Poison Control Center right away.

Directions

For sunscreen use:

- apply liberally 15 minutes before sun exposure
- use a water resistant sunscreen if swimming or sweating
- reapply at least every 2 hours
- children under 6 months: ask a doctor
- Sun protection measures. Spending time in the sun increases your risk of skin cancer and early skin aging. To decrease this risk, regularly use a sunscreen with a Broad Spectrum SPF of 15 or higher and other sun protection measures including:
  - limit time in the sun, especially from 10 a.m. - 2 p.m.
  - wear long-sleeve shirts, pants, hats, and sunglasses

Inactive ingredients

isododecane, disteardimonium hectorite, polymethylsilsesquioxane, caprylic/capric triglyceride, propylene carbonate, silica, trimethylsiloxysilicate, dipalmitoyl hydroxyproline, mangifera indica (mango) seed butter, carthamus tinctorius (safflower) seed oil, camellia oleifera leaf extract, acrylates copolymer, diacetyl boldine, calcium sodium borosilicate, calcium aluminum borosilicate, tin oxide, phenoxyethanol. may contain: mica, carmine, titanium dioxide, iron oxides, bismuth oxychloride, chromium hydroxide green, chromium oxide greens, ferric ferrocyanide, manganese violet, ultramarines.

Other information

Protect this product from excessive heat and direct sun

Questions or comments?

Call toll free 1-888-795-4747

Dist. by Bare Escentuals Beauty, Inc., SF, CA 94105 USA.

PRINCIPAL DISPLAY PANEL - 3 ml Tube Carton - Candlelit Peach

bareMinerals®
5IN1

BB advanced
performance
cream eyeshadow

BROAD SPECTRUM
SPF 15

3 ml / 0.10 fl oz.

PRINCIPAL DISPLAY PANEL - 3 ml Tube Carton - Radiant Sand

bareMinerals®
5IN1

BB advanced
performance
cream eyeshadow

BROAD SPECTRUM
SPF 15

3 ml / 0.10 fl oz.

PRINCIPAL DISPLAY PANEL - 3 ml Tube Carton - Soft Shell

bareMinerals®
5IN1

BB advanced
performance
cream eyeshadow

BROAD SPECTRUM
SPF 15

3 ml / 0.10 fl oz.

PRINCIPAL DISPLAY PANEL - 3 ml Tube Carton - Elegant Taupe

bareMinerals®
5IN1

BB advanced
performance
cream eyeshadow

BROAD SPECTRUM
SPF 15

3 ml / 0.10 fl oz.

PRINCIPAL DISPLAY PANEL - 3 ml Tube Carton - Soft Linen

bareMinerals®
5IN1

BB advanced
performance
cream eyeshadow

BROAD SPECTRUM
SPF 15

3 ml / 0.10 fl oz.

PRINCIPAL DISPLAY PANEL - 3 ml Tube Carton - Sweet Spice

bareMinerals®
5IN1

BB advanced
performance
cream eyeshadow

BROAD SPECTRUM
SPF 15

3 ml / 0.10 fl oz.

PRINCIPAL DISPLAY PANEL - 3 ml Tube Carton - Delicate Moss

bareMinerals®
5IN1

BB advanced
performance
cream eyeshadow

BROAD SPECTRUM
SPF 15

3 ml / 0.10 fl oz.

PRINCIPAL DISPLAY PANEL - 3 ml Tube Carton - Barely Nude

bareMinerals®
5IN1

BB advanced
performance
cream eyeshadow

BROAD SPECTRUM
SPF 15

3 ml / 0.10 fl oz.

PRINCIPAL DISPLAY PANEL - 3 ml Tube Carton - Blushing Pink

bareMinerals®
5IN1

BB advanced
performance
cream eyeshadow

BROAD SPECTRUM
SPF 15

3 ml / 0.10 fl oz.

PRINCIPAL DISPLAY PANEL - 3 ml Tube Carton - Divine Wine

bareMinerals®
5IN1

BB advanced
performance
cream eyeshadow

BROAD SPECTRUM
SPF 15

3 ml / 0.10 fl oz.